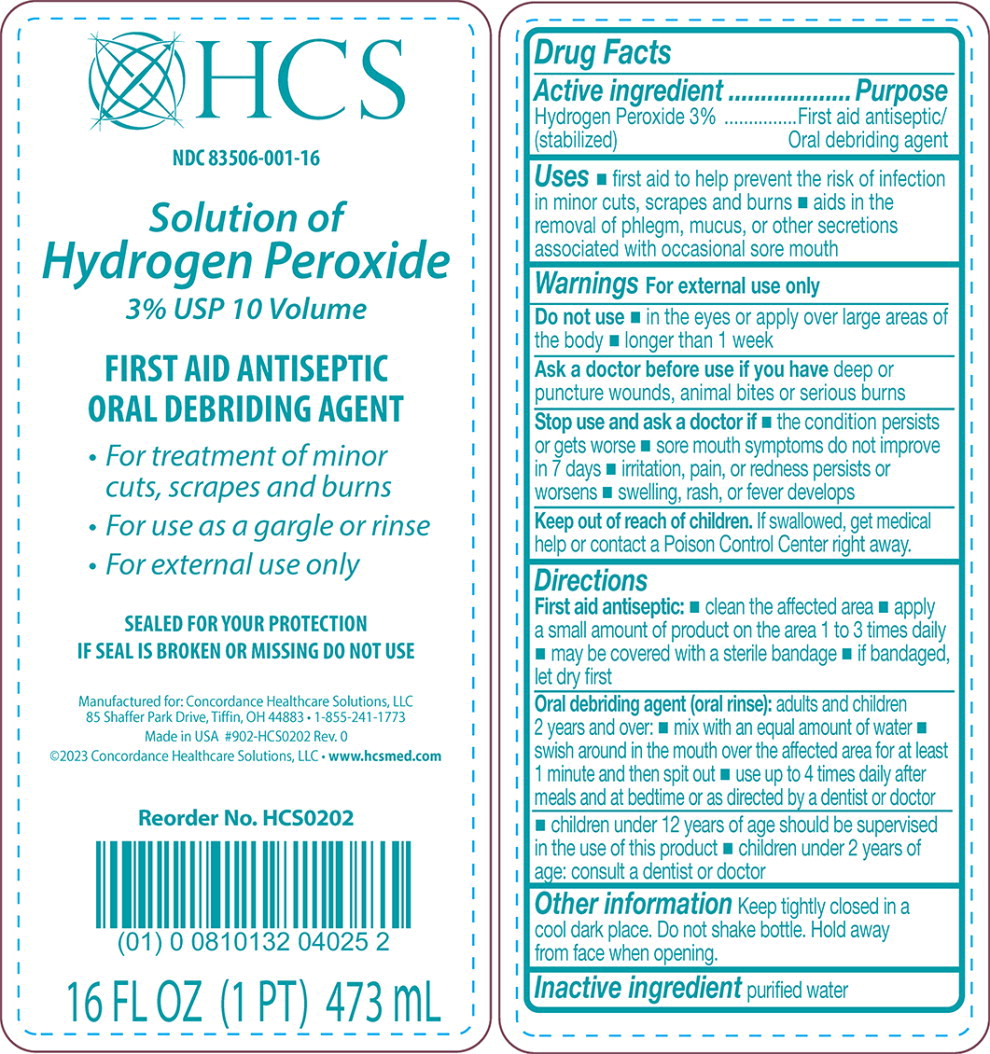 DRUG LABEL: HCS Hydrogen Peroxide 3%
NDC: 83506-001 | Form: LIQUID
Manufacturer: Concordance Healthcare Solutions, LLC.
Category: otc | Type: HUMAN OTC DRUG LABEL
Date: 20260112

ACTIVE INGREDIENTS: Hydrogen Peroxide 3 mL/100 mL
INACTIVE INGREDIENTS: Water

Hydrogen Peroxide
Drug Facts

Active ingredient

Hydrogen Peroxide (stabilized) 3%

Purpose

First aid antiseptic/Oral debriding agent

Uses

first aid to help prevent the risk of infection in minor cuts, scrapes and burns aids in the removal of phlegm, mucous, or other secretions associated with occasional sore mouth

Warnings

For external use only

Do not use

in the eyes or apply over large areas of the body

longer than 1 week

Ask a doctor before use if you have deep or puncture wounds, animal bites or serious burns

Stop use and ask a doctor if the condition persists or gets worse sore mouth symptoms do not improve in 7 days irritation, pain, or redness persists or worsens swelling, rash, or fever develops

Keep out of reach of children. If swallowed, get medical help or contact a Poison Control Center right away.

Directions

First aid antiseptic:

- clean the affected area
- apply a small amount of product on the area 1 to 3 times daily.
- May be covered with a sterile bandage; if bandaged, let dry first

Oral debriding agent (oral rinse): adults and children 2 years of age and over:

- mix with an equal amount of water
- swish around in the mouth over the affected area for at least 1 minute and then spit out

use up to 4 times daily after meals and at bedtime or as directed by a dentist or doctor

children under 12 years of age should be supervised in the use of this product children under 2 years of age: consult a dentist or doctor

Other information

Keep tightly closed in a cool dark place. Do not shake bottle. Hold away from face when opening.

Inactive ingredient

purified water

Principal Display Panel – 473 mL Bottle Label

HCS

NDC 83506-001-16

Solution of
Hydrogen Peroxide
3% USP 10 Volume

FIRST AID ANTISEPTIC

ORAL DEBRIDING AGENT

- For treatment of minor
  cuts, scrapes, and burns
- For use as a gargle or rinse
- For external use only

SEALED FOR YOUR PROTECTION

IF THE SEAL IS BROKEN OR MISSING DO NOT USE

16 FL OZ (1 PT) 473 mL